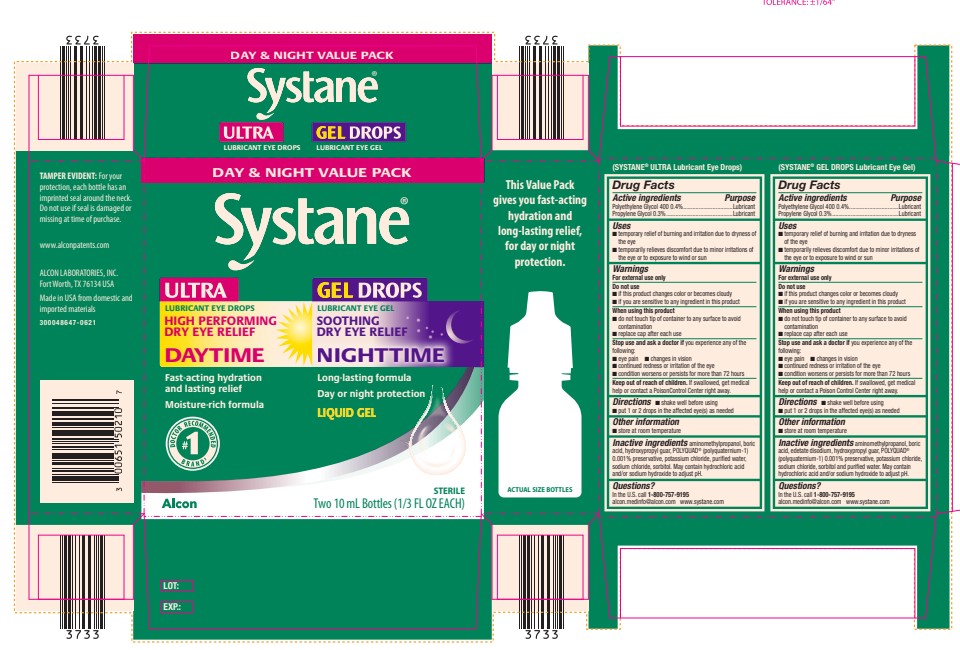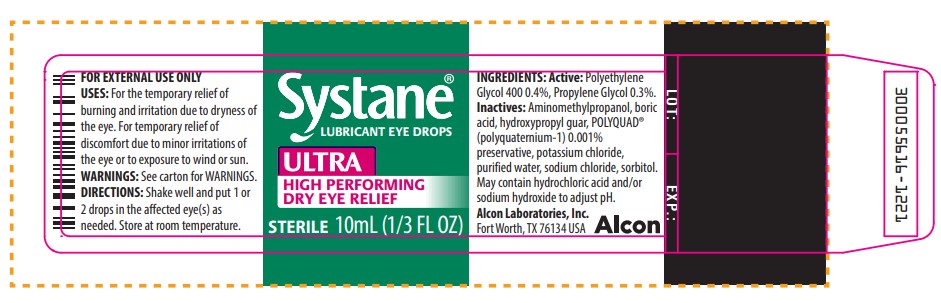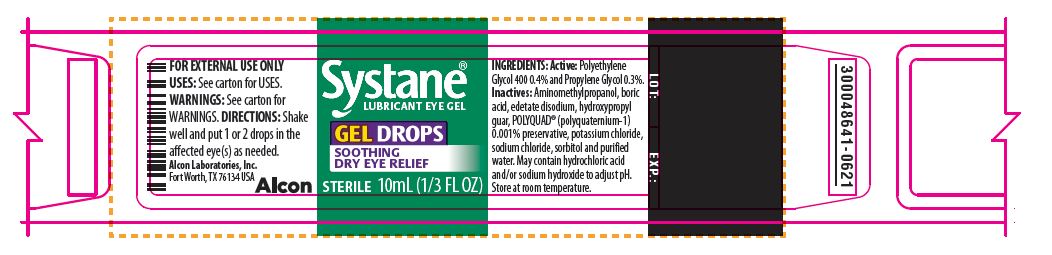 DRUG LABEL: Systane Day and Night Value Pack
NDC: 0065-1502 | Form: KIT | Route: OPHTHALMIC
Manufacturer: Alcon Laboratories, Inc.
Category: otc | Type: HUMAN OTC DRUG LABEL
Date: 20231215

ACTIVE INGREDIENTS: Polyethylene Glycol 400 4 mg/1 mL; Propylene Glycol 3 mg/1 mL; Polyethylene Glycol 400 4 mg/1 mL; Propylene Glycol 3 mg/1 mL
INACTIVE INGREDIENTS: Aminomethylpropanol; Boric Acid; Guar Gum; Polidronium Chloride; Potassium Chloride; Water; Sodium Chloride; Hydrochloric Acid; Sodium Hydroxide; Aminomethylpropanol; Boric Acid; Edetate Disodium; Guar Gum; Polidronium Chloride; Potassium Chloride; Sodium Chloride; Sorbitol; Water; Hydrochloric Acid; Sodium Hydroxide

Drug Facts

SYSTANE® ULTRA Lubricant Eye Drops

Active ingredients | Purpose
Polyethylene Glycol 400 0.4% | Lubricant
Propylene Glycol 0.3% | Lubricant

Uses

- temporary relief of burning and irritation due to dryness of the eye
- temporarily relieves discomfort due to minor irritations of the eye or to exposure to wind or sun

Warnings

For external use only

Do not use

- if this product changes color or becomes cloudy
- if you are sensitive to any ingredient in this product

When using this product

- do not touch tip of container to any surface to avoid contamination
- replace cap after each use

Stop use and ask a doctor if you experience any of the following:

- eye pain
- changes in vision
- continued redness or irritation of the eye
- condition worsens or persists for more than 72 hours

Keep out of reach of children. If swallowed, get medical help or contact a Poison Control Center right away.

Directions

- shake well before using
- put 1 or 2 drops in the affected eye(s) as needed

Other information

- store at room temperature

Inactive ingredients

aminomethylpropanol, boric acid, hydroxypropyl guar, POLYQUAD® (polyquaternium-1) 0.001% preservative, potassium chloride, purified water, sodium chloride, sorbitol. May contain hydrochloric acid and/or sodium hydroxide to adjust pH.

Questions?

In the U.S. call 1-800-757-9195
alcon.medinfo@alcon.com
www.systane.com

SYSTANE® GEL DROPS Lubricant Eye Gel

Active ingredients | Purpose
Polyethylene Glycol 400 0.4% | Lubricant
Propylene Glycol 0.3% | Lubricant

Uses

- temporary relief of burning and irritation due to dryness of the eye
- temporarily relieves discomfort due to minor irritations of the eye or to exposure to wind or sun

Warnings

For external use only

Do not use

- if this product changes color or becomes cloudy
- if you are sensitive to any ingredient in this product

When using this product

- do not touch tip of container to any surface to avoid contamination
- replace cap after each use

Stop use and ask a doctor if you experience any of the following:

- eye pain
- changes in vision
- continued redness or irritation of the eye
- condition worsens or persists for more than 72 hours

Keep out of reach of children. If swallowed, get medical help or contact a Poison Control Center right away.

Directions

- shake well before using
- put 1 or 2 drops in the affected eye(s) as needed

Other information

- store at room temperature

Inactive ingredients

aminomethylpropanol, boric acid, edetate disodium, hydroxypropyl guar, POLYQUAD® (polyquaternium-1) 0.001% preservative, potassium chloride, sodium chloride, sorbitol and purified water. May contain hydrochloric acid and/or sodium hydroxide to adjust pH.

Questions?

In the U.S. call toll free 1-800-757-9195
alcon.medinfo@alcon.com
www.systane.com

PACKAGE LABEL.PRINCIPAL DISPLAY PANEL

DAY & NIGHT VALUE PACK
Systane®
ULTRA
LUBRICANT EYE DROPS
HIGH PERFORMING DRY EYE RELIEF
DAYTIME
Fast-acting hydration and lasting relief
Moisture-rich formula
#1 DOCTOR RECOMMENDED BRAND^1
GEL DROPS
LUBRICANT EYE GEL
SOOTHING DRY EYE RELIEF
NIGHTTIME
Long-lasting formula
Day or night protection
LIQUID GEL
STERILE
Two 10 mL Bottles (1/3 FL OZ EACH)
Alcon®
This Value Pack
gives you fast-acting
hydration and
long-lasting relief,
for day or night
protection.
ACTUAL SIZE BOTTLES
TAMPER EVIDENT: For your
protection, each bottle has an
imprinted seal around the neck.
Do not use if seal is damaged or
missing at time of purchase.
www.alconpatents.com
ALCON LABORATORIES, INC.
Fort Worth, TX 76134 USA
Made in USA from domestic and
foreign materials
300048647-0621
LOT:
EXP.:

Systane® ULTRA
LUBRICANT EYE DROPS
HIGH PERFORMANCE
STERILE
10 mL (1/3 FL OZ)
FOR EXTERNAL USE ONLY.
INDICATIONS: For the temporary relief of burning and irritation due to dryness of the eye.
DIRECTIONS: Shake well and instill 1 or 2 drops in the affected eye(s) as needed.
WARNINGS: See carton for WARNINGS.
INGREDIENTS:
Actives: Polyethylene Glycol 400 0.4%, Propylene Glycol 0.3%.
Inactives: Aminomethylpropanol, boric acid, hydroxypropyl guar, POLYQUAD® (polyquaternium-1) 0.001% preservative, potassium chloride, purified water, sodium chloride, sorbitol. May contain hydrochloric acid and/or sodium hydroxide to adjust pH.
Store at room temperature.
Alcon Laboratories, Inc.
Fort Worth, TX 76134 USA
Alcon®
LOT:
EXP.:
300055616-1221

Systane® GEL DROPS
LUBRICANT EYE GEL
Soothing Dry Eye Relief
STERILE
10 mL (1/3 FL OZ)
FOR EXTERNAL USE ONLY.
Uses: See carton for USES.
WARNINGS: See carton for WARNINGS.
Directions: Shake well and put 1 or 2 drops in the affected eye(s) as needed.
INGREDIENTS:
Actives: Polyethylene Glycol 0.4% and Propylene Glycol 0.3%.
Inactives: Aminomethylpropanol, boric acid, edetate disodium, hydroxypropyl guar, POLYQUAD® (polyquaternium-1) 0.001% preservative, potassium chloride, sodium chloride, sorbitol and purified water. May contain hydrochloric acid and/or sodium hydroxide to adjust pH.
Store at room temperature.
Alcon Laboratories, Inc.
Fort Worth, TX 76134 USA
Alcon
LOT:
EXP.:
300048641-0621